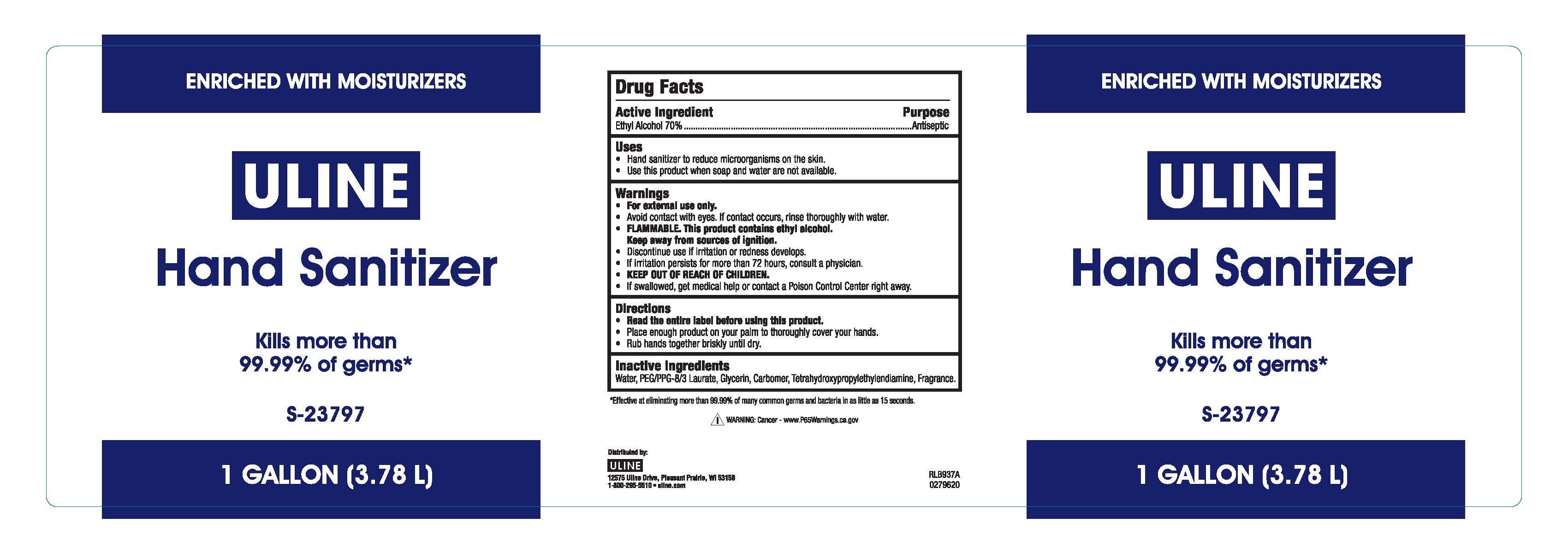 DRUG LABEL: Uline Hand Sanitizer
NDC: 69790-801 | Form: GEL
Manufacturer: Uline
Category: otc | Type: HUMAN OTC DRUG LABEL
Date: 20241118

ACTIVE INGREDIENTS: ALCOHOL 0.7 mL/1 mL
INACTIVE INGREDIENTS: WATER; CARBOMER INTERPOLYMER TYPE A (ALLYL SUCROSE CROSSLINKED); DIMETHICONE PEG-8 LAURATE; GLYCERIN; EDETOL; ALOE BARBADENSIS LEAF JUICE; OCTOXYNOL-13; CYCLOHEXANE; HEXYL SALICYLATE; POLYETHYLENE GLYCOL, UNSPECIFIED; LINALOOL; NEROL; .GAMMA.-TERPINENE; LIMONENE, (+)-; .ALPHA.-PINENE; ALLYL CYCLOHEXANEPROPIONATE; GERANIOL; CITRONELLOL; PROPYLENE OXIDE; ACRYLIC ACID; METHYL DIHYDROJASMONATE (SYNTHETIC)

Uline Hand Sanitizer

Active Ingredient

Ethyl Alcohol 70%

Uses

• Hand sanitizer to reduce microorganisms on the skin.

• Use this product when soap and water are not available.

Purpose

Antiseptic

Warnings

• For external use only.

• Avoid contact with eyes. If contact occurs, rinse thoroughly with water.

• FLAMMABLE. This product contains ethyl alcohol. Keep away from

sources of ignition.

• Discontinue use if irritation or redness develops.

• If irritation persists for more than 72 hours, consult a physician.

• KEEP OUT OF REACH OF CHILDREN.

• If swallowed, get medical help or contact a Poison Control Center right away.

Directions

• Read the entire label before using this product.

• Place enough product on your palm to thoroughly cover your hands.

• Rub hands together briskly until dry.

Inactive Ingredients

Water, PEG/PPG-8/3 Laurate, Gycerin, Carbomer, Tetrahydroxypropylethylendiamine, Fragrance.

Warnings

KEEP OUT OF REACH OF CHILDREN.

Principal Display Panel

3780 ml 69790-801-04